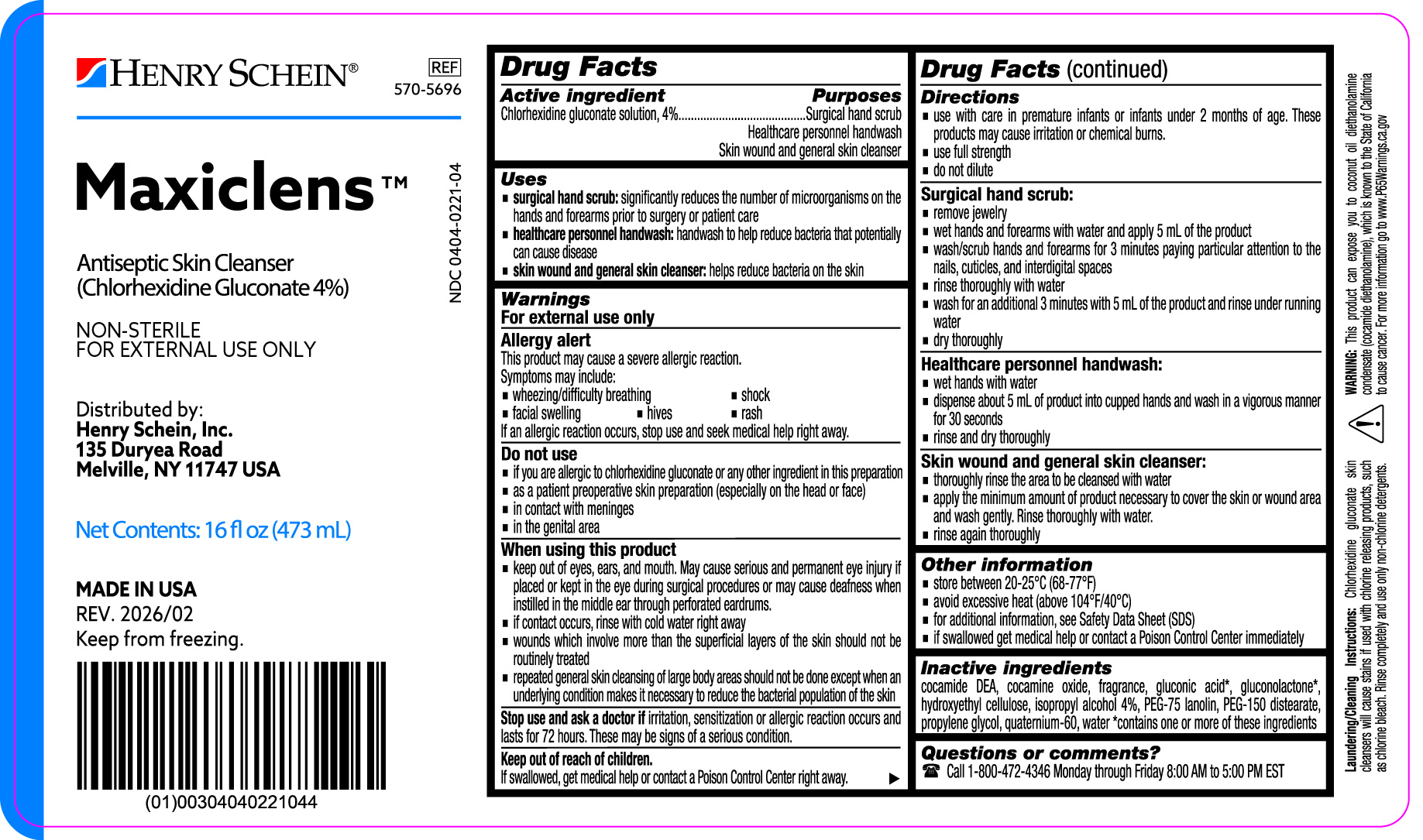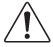 DRUG LABEL: Maxiclens Chlorhexidine Gluconate Liquid Solution, 4%
NDC: 0404-0221 | Form: SOLUTION
Manufacturer: Henry Schein, Inc.
Category: otc | Type: HUMAN OTC DRUG LABEL
Date: 20260217

ACTIVE INGREDIENTS: CHLORHEXIDINE GLUCONATE 40 mg/1 mL
INACTIVE INGREDIENTS: COCO DIETHANOLAMIDE; WATER; GLUCONIC ACID; QUATERNIUM-33; GLUCONOLACTONE; PEG-75 LANOLIN; PEG-150 DISTEARATE; PROPYLENE GLYCOL; ISOPROPYL ALCOHOL; COCAMINE OXIDE; HYDROXYETHYL CELLULOSE (3000 CPS AT 1%)

MaxiclensTM 16 fl oz (473 mL)

Active ingredient

Chlorhexidine gluconate solution, 4%

Purposes

Surgical hand scrub

Healthcare personnel handwash

Skin wound and general skin cleanser

Uses

surgical hand scrub:significantly reduces the number of microorganisms on the hands and forearms prior to surgery or patient care
healthcare personnel handwash:handwash to help reduce bacteria that potentially can cause disease
skin wound and general skin cleanser:helps reduce bacteria on the skin

Warnings
For external use only

Allergy alert

This product may cause a severe allergic reaction.

Symptoms may include:

- wheezing/difficulty breathing
- shock
- facial swelling
- hives
- rash

If an allergic reaction occurs, stop use and seek medical help right away.

Do not use

- if you are allergic to chlorhexidine gluconate or any other ingredient in this preparation
- as a patient preoperative skin preparation (especially on the head or face)
- in contact with meninges
- in the genital area

When using this product

- keep out of eyes, ears, and mouth. May cause serious and permanent eye injury if placed or kept in the eye during surgical procedures or may cause deafness when instilled in the middle ear through perforated eardrums.
- if contact occurs, rinse with cold water right away
- wounds which involve more than the superficial layers of the skin should not be routinely treated
- repeated general skin cleansing of large body areas should not be done except when an underlying condition makes it necessary to reduce the bacterial population of the skin

Stop use and ask a doctor ifirritation, sensitization or allergic reaction occurs and lasts for 72 hours. These may be signs of a serious condition.

Keep out of reach of children.
If swallowed, get medical help or contact a Poison Control Center right away.

Directions

- use with care in premature infants or infants under 2 months of age. These products may cause irritation or chemical burns.
- use full strength
- do not dilute

Surgical hand scrub:

- remove jewelry
- wet hands and forearms with water and apply 5 mL of the product
- wash/scrub hands and forearms for 3 minutes paying particular attention to the nails, cuticles, and interdigital spaces
- rinse thoroughly with water
- wash for an additional 3 minutes with 5 mL of the product and rinse under running water
- dry thoroughly

Healthcare personnel handwash:

- wet hands with water
- dispense about 5 mL of product into cupped hands and wash in a vigorous manner for 30 seconds
- rinse and dry thoroughly

Skin wound and general skin cleanser:

- thoroughly rinse the area to be cleansed with water
- apply the minimum amount of product necessary to cover the skin or wound area and wash gently. Rinse thoroughly with water.
- rinse again thoroughly

Other information

- store between 20-25°C (68-77°F)
- avoid excessive heat (above 104°F/40°C)
- for additional information, see Safety Data Sheet (SDS)
- if swallowed get medical help or contact a Poison Control Center immediately

Inactive ingredients

cocamide DEA, cocamine oxide, fragrance, gluconic acid*, gluconolactone*, hydroxyethyl cellulose, isopropyl alcohol 4%, PEG-75 lanolin, PEG-150 distearate, propylene glycol, quaternium-60, water

*contains one or more of these ingredients

Questions or comments?

Call 1-800-472-4346 Monday through Friday 8:00 AM to 5:00 PM EST

PACKAGE LABEL

NDC 0404-0221-04

MaxiclensTM

Antiseptic Skin Cleanser

(Chlorhexidine Gluconate 4%)

NON-STERILE

FOR EXTERNAL USE ONLY

Distributed By

HENRY SCHEIN INC.

135 Duryea Road

Melville, NY 11747 USA

Net Contents: 16 fl oz (473 mL)

Made in U.S.A.

Laundering/Cleaning Instructions:Chlorhexidine gluconate skin cleansers will cause stains if used with chlorine releasing products, such as chlorine bleach. Rinse completely and use only non-chlorine detergents.

WARNING:This product can expose you to coconut oil diethanolamine condensate (cocamide diethanolamine), which is known to the State of California to cause cancer. For more information go to www.P65Warnings.ca.gov

Keep from freezing.